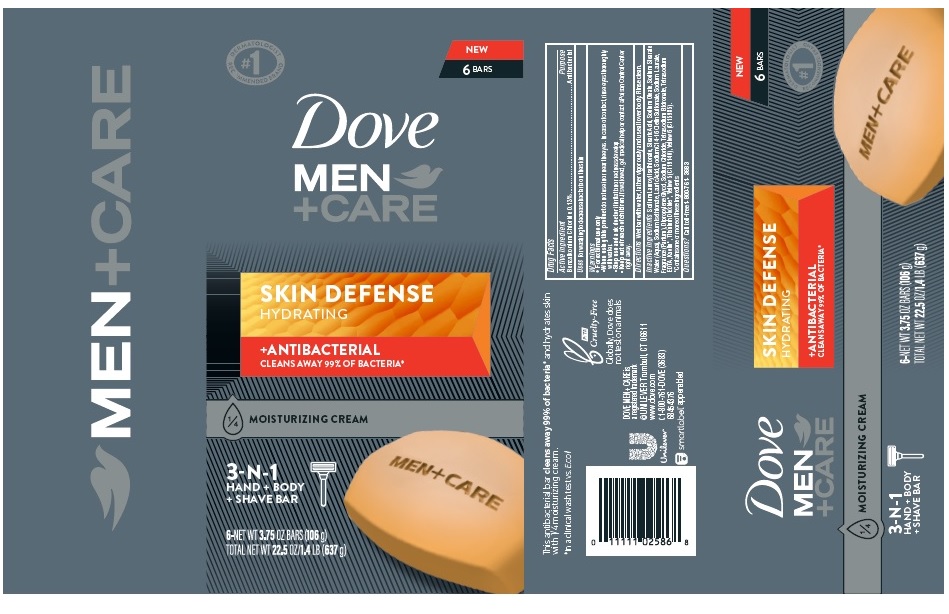 DRUG LABEL: Dove
NDC: 64942-1846 | Form: SOAP
Manufacturer: Conopco Inc. d/b/a/ Unilever
Category: otc | Type: HUMAN OTC DRUG LABEL
Date: 20241107

ACTIVE INGREDIENTS: BENZALKONIUM CHLORIDE 0.13 g/100 g
INACTIVE INGREDIENTS: SODIUM C14-16 OLEFIN SULFONATE; FD&C YELLOW NO. 6; SODIUM LAUROYL ISETHIONATE; SODIUM OLEATE; SODIUM STEARATE; SODIUM ISETHIONATE; LAURIC ACID; SODIUM LAURATE; DIPROPYLENE GLYCOL; TITANIUM DIOXIDE; ETIDRONATE TETRASODIUM; KAOLIN; FD&C YELLOW NO. 5; STEARIC ACID; SODIUM CHLORIDE; WATER; EDETATE SODIUM

Dove Men +Care Skin Defense Antibacterial 3-N-1 Hand + Body + Shave Bar

DOVE MEN +CARE SKIN DEFENSE ANTIBACTERIAL 3-N-1 HAND + BODY + SHAVE BAR - Benzalkonium Chloride soap

Dove Men +Care Skin Defense Antibacterial 3-N-1 Hand + Body + Shave Bar

Drug Facts

Active ingredient

Benzalkonium Chloride (0.13%)

Purpose

Antibacterial

Uses

For washing to decrease bacteria on the skin

Warnings

• For external use only
• When using this product do not use in or near the eyes. In case of contact, rinse eyes thoroughly with wate r
• Stop use and ask doctor if irritation or redness develop.

• Keep out of reach of children except under adult supervision.

If swallowed, get medical help or contact a poison control Center right away.

Directions

Wet bar with water, lather vigorously and use all over body. Rinse clean.

Inactive ingredients

Sodium Lauroyl Isethionate, Stearic Acid, Sodium Oleate, Sodium Stearate, Water (Aqua), Sodium Isethionate, Lauric Acid, Sodium C14-16 Olefin Sulfonate, Sodium Laurate, Fragrance (Parfum), Dipropylene Glycol, Sodium Chloride, Tetrasodium Etidronate, Tetrasodium EDTA, Kaolin*, Titanium Dioxide*, Yellow 5 (CI 19140), Yellow 6 (CI 15985). *Contains one or more of these ingredients

Questions or Comments?

Call toll-free 1-800-761-3683